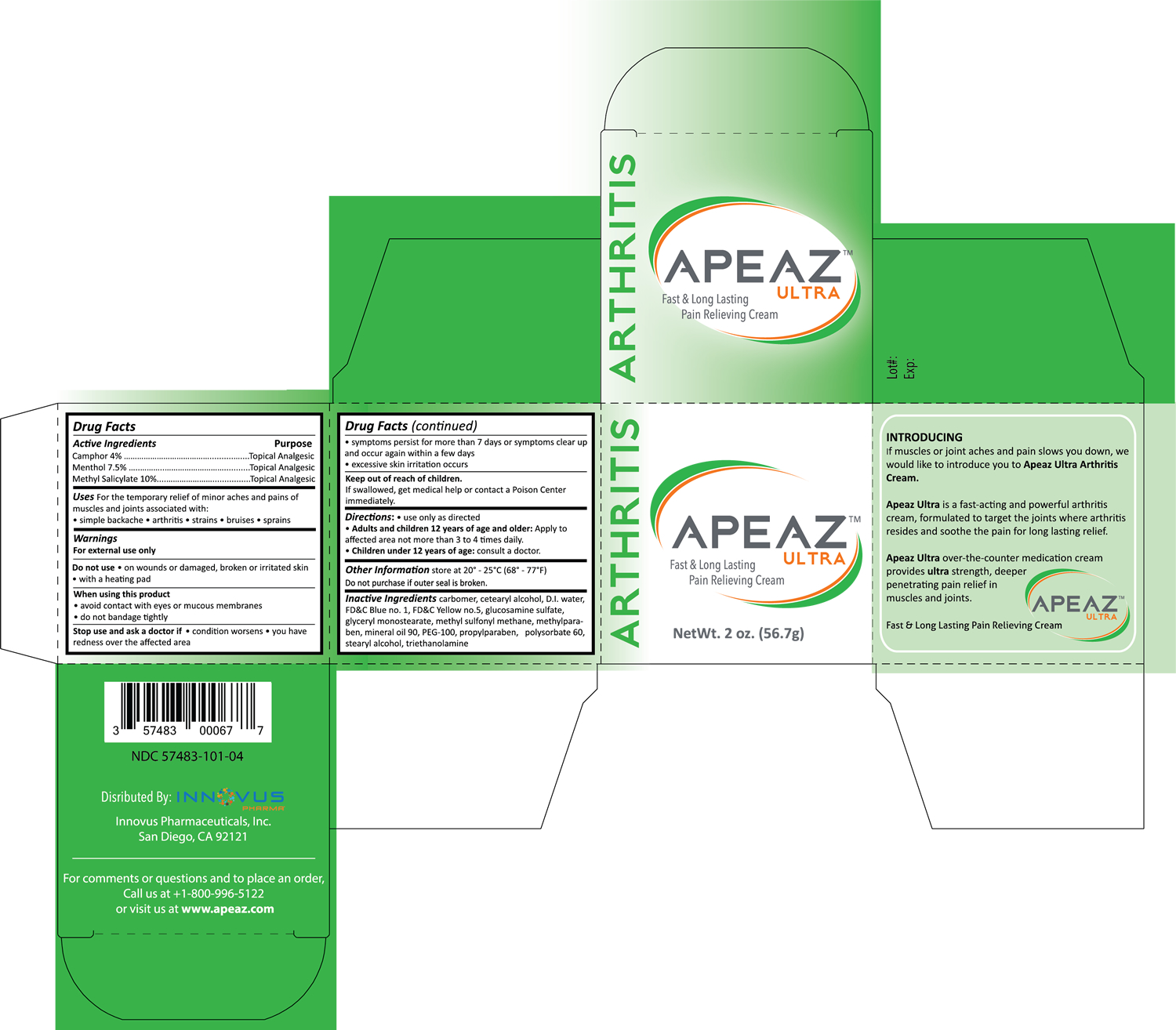 DRUG LABEL: Apeaz Ultra
NDC: 57483-101 | Form: CREAM
Manufacturer: Innovus Pharmaceuticals, Inc.
Category: otc | Type: HUMAN OTC DRUG LABEL
Date: 20241227

ACTIVE INGREDIENTS: CAMPHOR (SYNTHETIC) 4.0 mg/1 g; MENTHOL 7.5 mg/1 g; METHYL SALICYLATE 10 mg/1 g
INACTIVE INGREDIENTS: WATER; CETOSTEARYL ALCOHOL; STEARYL ALCOHOL; GLYCERYL MONOSTEARATE; PEG-100 STEARATE; MINERAL OIL; METHYLPARABEN; PROPYLPARABEN; POLYSORBATE 60; DIMETHYL SULFONE; GLUCOSAMINE SULFATE; TROLAMINE; CARBOMER 940; FD&C YELLOW NO. 5; FD&C BLUE NO. 1

Apeaz Ultra

Active ingredient

Camphor 4%

Menthol 7.5%

Methyl Salicylate 10%

Purpose

Topical analgesic

Uses

For the temporary relief of minor aches and pains of muscles and joints associated with:

- simple backache
- arthritis
- strains
- bruises
- sprains

Warnings

For external use only.

Do not use

- on wounds or damaged, broken or irritated skin
- with a heating pad

When using this product

- avoid contact with eyes or mucous membranes
- do not bandage tightly

Stop use and ask a doctor

- condition worsens or symptoms persist for more than 7 days
- symptoms clear up and occur again within a few days
- excessive skin irritation occurs

Keep out of reach of children

If swallowed, get medical help or contact a Poison Center immediately

Directions

- use only as directed
- adults and children 12 years of age and older: apply to affected area not more than 3 to 4 times daily
- children under 12 years of age: ask a doctor

Other information

Store at 20° to 25°C (68° to 77°F)

Do not purchase if outer seal is broken

Inactive ingredients

carbomer, cetearyl alcohol, water, FD&C Blue no 1, FD&C Yellow no 5, glucosamine sulfate, glyceryl monostearate, methyl sulfonyl methane, methylparaben, mineral oil 90, PEG-100, propylparaben, polysorbate 60, stearyl alcohol, triethanolamine